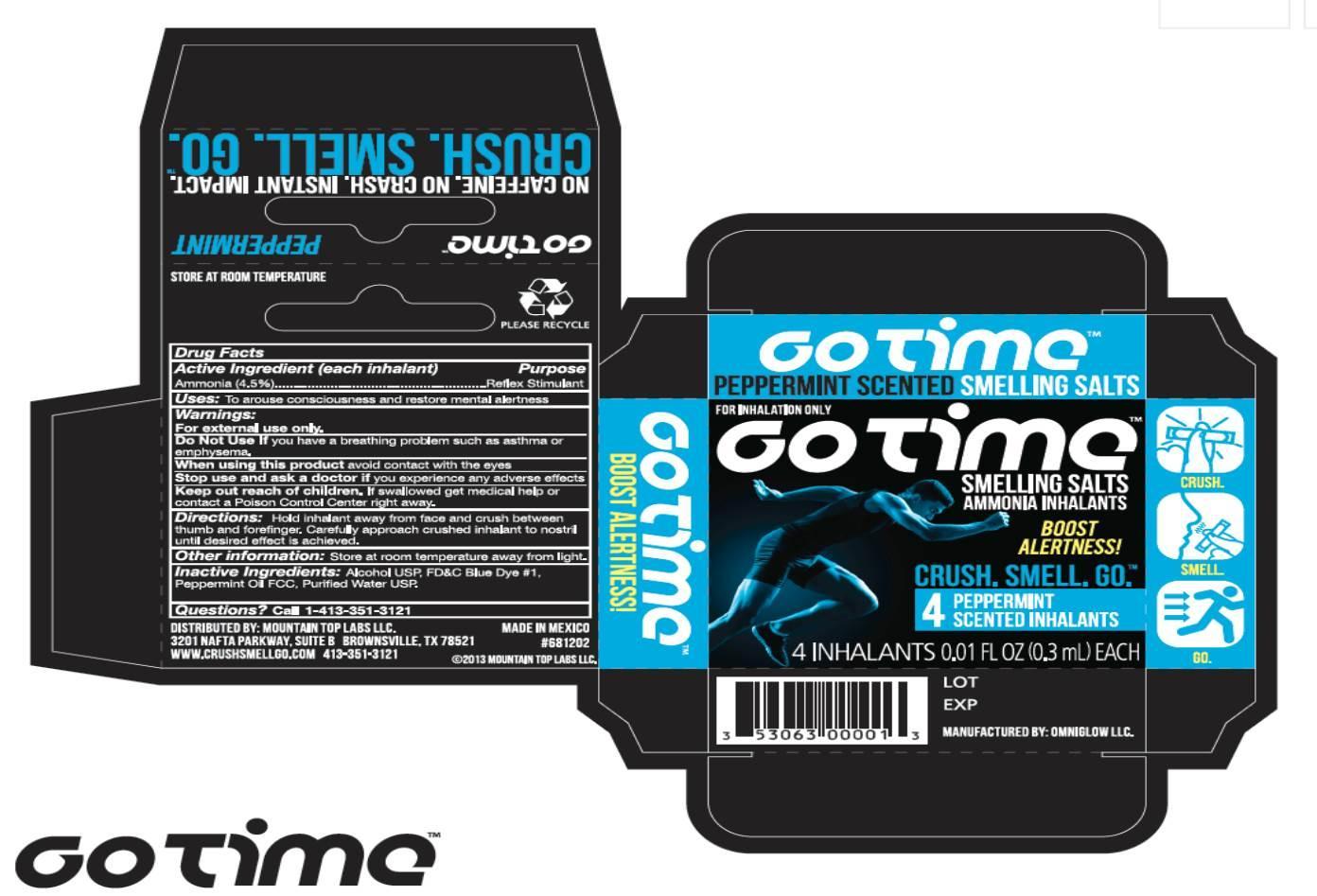 DRUG LABEL: GO TIME
NDC: 53063-1111 | Form: INHALANT
Manufacturer: Mountain Top Labs, LLC
Category: otc | Type: HUMAN OTC DRUG LABEL
Date: 20130319

ACTIVE INGREDIENTS: AMMONIA 0.013 mL/0.3 mL
INACTIVE INGREDIENTS: ALCOHOL; FD&C BLUE NO. 1; PEPPERMINT OIL; WATER

Drug Facts

Active ingredient (each inhalant)

Ammonia 4.5%

Purpose

Reflex Stimulant

Uses

To arouse consciousness and restore mental alertness.

Warnings

For external use only

Do not use if you have breathing problems such as asthma or emphysema.

When using this product avoid contact with the eyes.

Stop use and ask a doctor if you experience any adverse effects.

Keep out of reach of children. If swallowed, get medical help or contact a Poison Control Center right away.

Directions

Hold inhalant away from face and crush between thumb and forefinger. Carefully approach crushed inhalant to nostril until desired effect is achieved.

Other information

Store at room temperature away from light.

Inactive ingredients

Alcohol USP, FD and C Blue Dye #1, Peppermint Oil, Purified Water USP

Questions?

Call 1-413-351-3121

PACKAGE LABEL

NDC 53063-1111-1